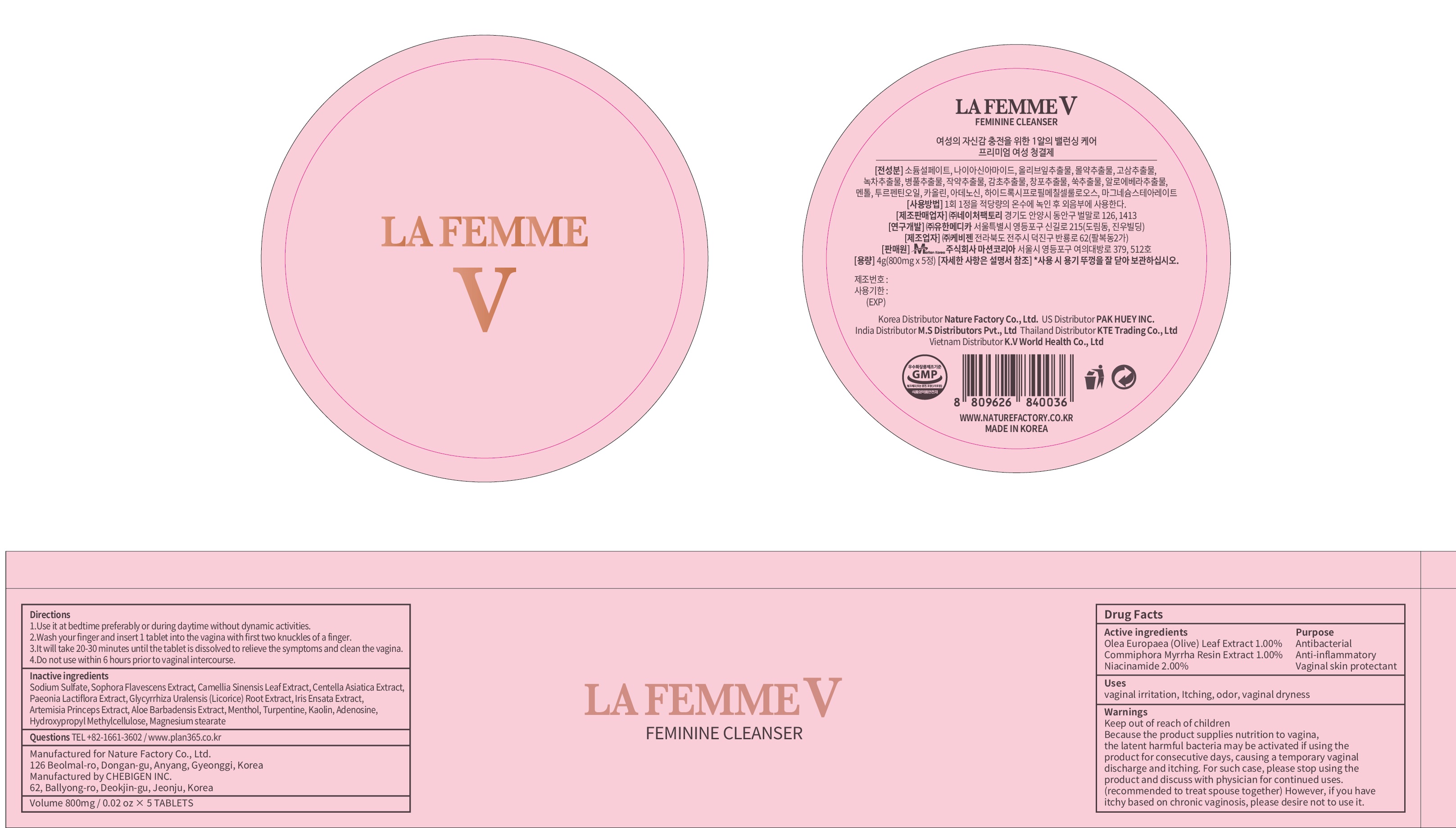 DRUG LABEL: LA FEMME V Feminine Cleanser
NDC: 72798-010 | Form: TABLET
Manufacturer: Nature Factory Co., Ltd.
Category: otc | Type: HUMAN OTC DRUG LABEL
Date: 20190130

ACTIVE INGREDIENTS: OLEA EUROPAEA LEAF 8.0 mg/800 mg; MYRRH 8.0 mg/800 mg; NIACINAMIDE 16.0 mg/800 mg
INACTIVE INGREDIENTS: Sodium Sulfate

ACTIVE INGREDIENT

Active ingredients:
Olea Europaea (Olive) Leaf Extract 1.00%
Commiphora Myrrha Resin Extract 1.00%
Niacinamide 2.00%

INACTIVE INGREDIENT

Inactive ingredients:
Sodium Sulfate, Sophora Flavescens Extract, Camellia Sinensis Leaf Extract, Centella Asiatica Extract, Paeonia Lactiflora Extract, Glycyrrhiza Uralensis (Licorice) Root Extract, Iris Ensata Extract, Artemisia Princeps Extract, Aloe Barbadensis Extract, Menthol, Turpentine, Kaolin, Adenosine, Hydroxypropyl Methylcellulose, Magnesium stearate

PURPOSE

Antibacterial
Anti-inflammatory
Vaginal skin protectant

WARNINGS

Keep out of reach of children
Because the product supplies nutrition to vagina, the latent harmful bacteria may be activated if using the product for consecutive days, causing a temporary vaginal discharge and itching. For such case, please stop using the product and discuss with physician for continued uses.
(recommended to treat spouse together) However, if you have itchy based on chronic vaginosis, please desire not to use it.

KEEP OUT OF REACH OF CHILDREN

Uses

Uses: vaginal irritation, Itching, odor, vaginal dryness

Directions

1.Use it at bedtime preferably or during daytime without dynamic activities.

2.Wash your finger and insert 1 tablet into the vagina with first two knuckles of a finger.

3.It will take 20-30 minutes until the tablet is dissolved to relieve the symptoms and clean the vagina. 4.Do not use within 6 hours prior to vaginal intercourse.